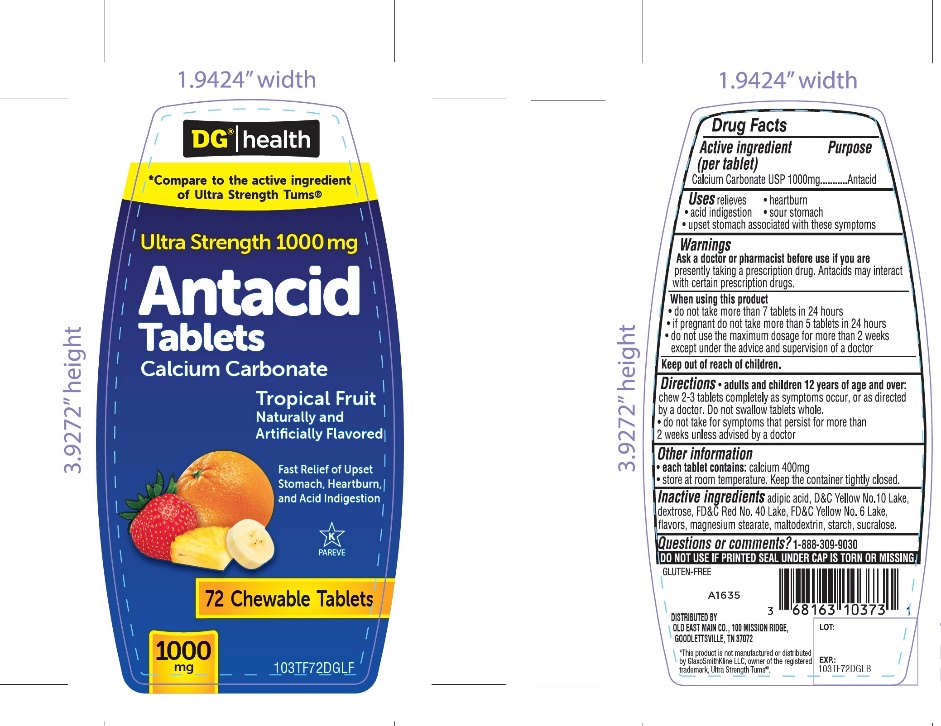 DRUG LABEL: DG HEALTH

NDC: 55910-083 | Form: TABLET, CHEWABLE
Manufacturer: DOLGENCORP, LLC
Category: otc | Type: HUMAN OTC DRUG LABEL
Date: 20250822

ACTIVE INGREDIENTS: CALCIUM CARBONATE 1000 mg/1 1
INACTIVE INGREDIENTS: ADIPIC ACID; D&C YELLOW NO. 10; DEXTROSE, UNSPECIFIED FORM; FD&C RED NO. 40; FD&C YELLOW NO. 6; MAGNESIUM STEARATE; MALTODEXTRIN; STARCH, CORN; SUCRALOSE

DG Health Ultra strength antacid calcium carbonate Tropical Fruit 72 Chewable Tablets

Active ingredient (per tablet)

Calcium Carbonate USP 1000mg

Purpose

Antacid

Uses

relieves

- heartburn
- acid indigestion
- sour stomach
- upset stomach associated with these symptoms

Warnings

Ask a doctor or pharmacist before use if you arepresently taking a prescription drug. Antacids may interact with certain prescription drugs.

When using this product

- do not take more than 7 tablets in 24 hours
- if pregnant do not take more than 5 tablets in 24 hours
- do not use the maximum dosage for more than 2 weeks except under the advice and supervision of a doctor.

Directions

- adults and children 12 years of age and over:chew 2-3 tablets as symptoms occur, or as directed by a doctor. Do not swallow tablets whole.
- do not take for symptoms that persist for more than 2 weeks unless advised by a doctor

Other information

- each tablet contains: calcium 400mg
- store at room temperature. Keep the container tightly closed

Inactive ingredients

adipic acid, D&C yellow 10 lake, dextrose, FD&C red 40 lake, FD&C yellow 6 lake, flavors, magnesium stearate, maltodextrin, starch, sucralose

Questions or comments?

1-888-309-9030

DO NOT USE IF PRINTED SEAL UNDER CAP IS TORN OR MISSING

Package/Label Principal Display Panel

NDC 55910-083-50

*Compare to the active ingredient of Ultra Strength Tums®

Ultra Strength 1000

Antacid Tablets

Calcium Carbonate

Tropical Fruit Flavor

Naturally and Artificially Flavored

Fast Relief of Upset Stomach, Heartburn, and Acid Indigestion

72 Chewable Tablets

Gluten- Free

Distributed by

OLD EAST MAIN CO.

100 MISSION RIDGE,

GOODLETTSVILLE,

TN 37072 USA

*This product is not manufactured or distributed by GlaxoSmithKline LLC, owner of the registered trademark, Ultra Strength Tums®.